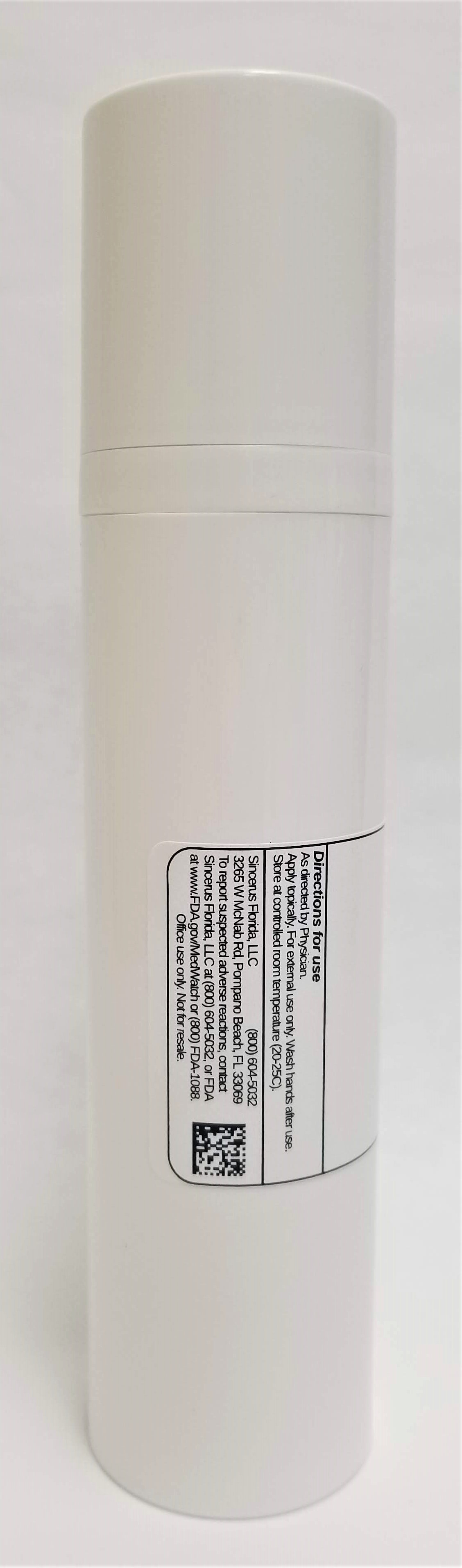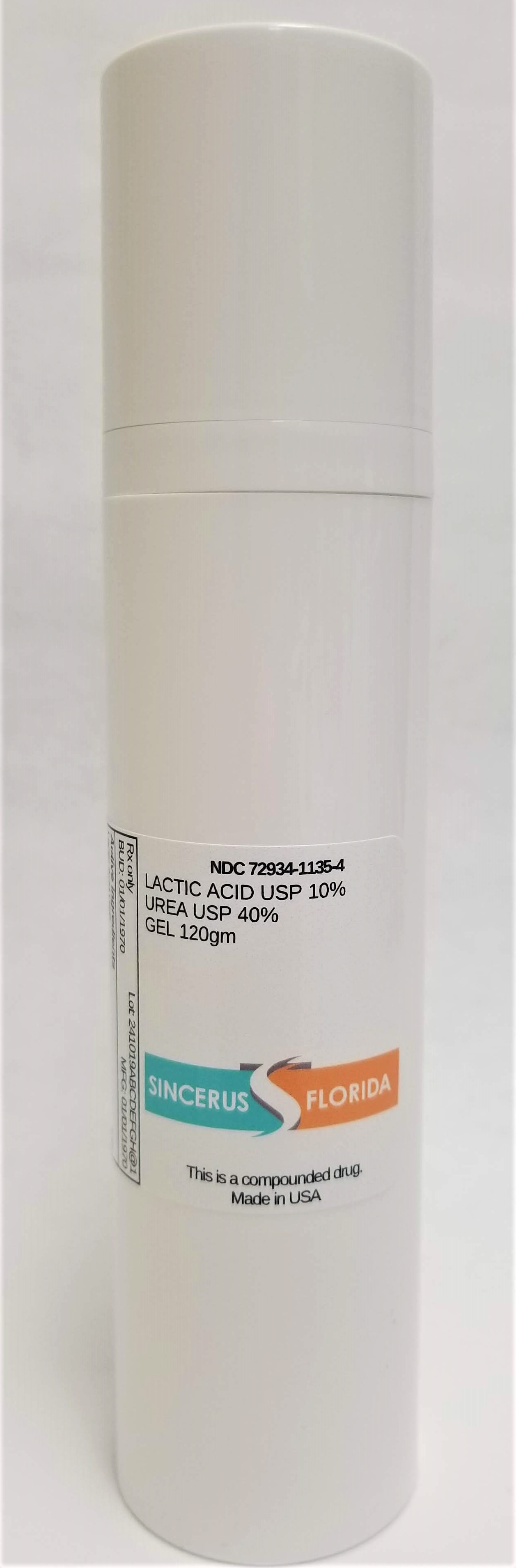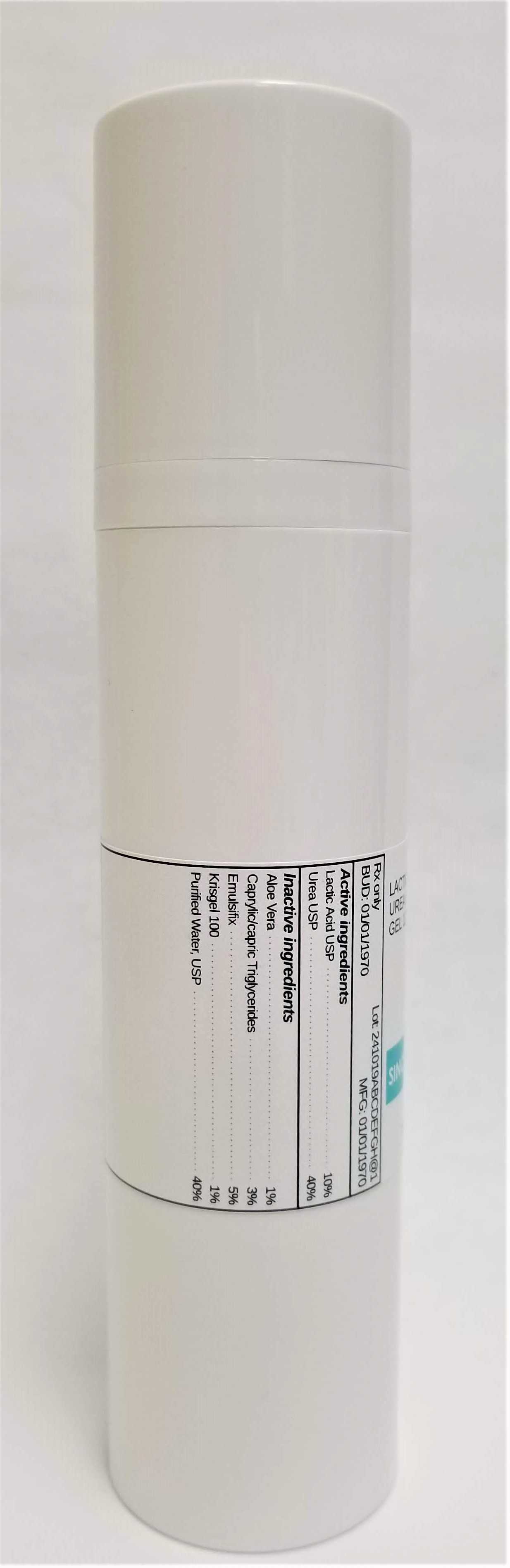 DRUG LABEL: LACTIC ACID 10% / UREA 40%
NDC: 72934-1135 | Form: GEL
Manufacturer: Sincerus Florida, LLC
Category: prescription | Type: HUMAN PRESCRIPTION DRUG LABEL
Date: 20190517

ACTIVE INGREDIENTS: UREA 40 g/100 g; LACTIC ACID 10 g/100 g

LACTIC ACID 10% / UREA 40%